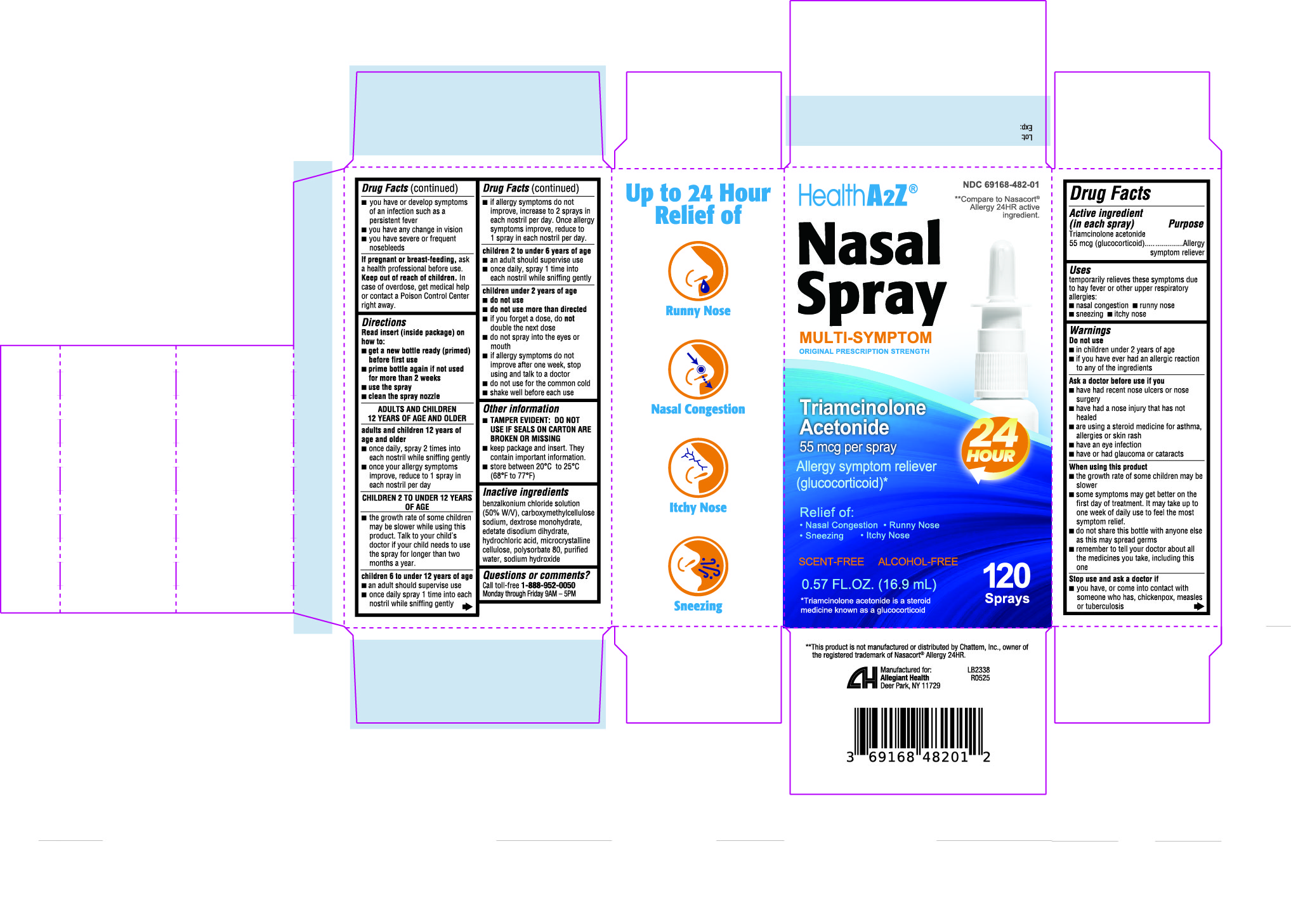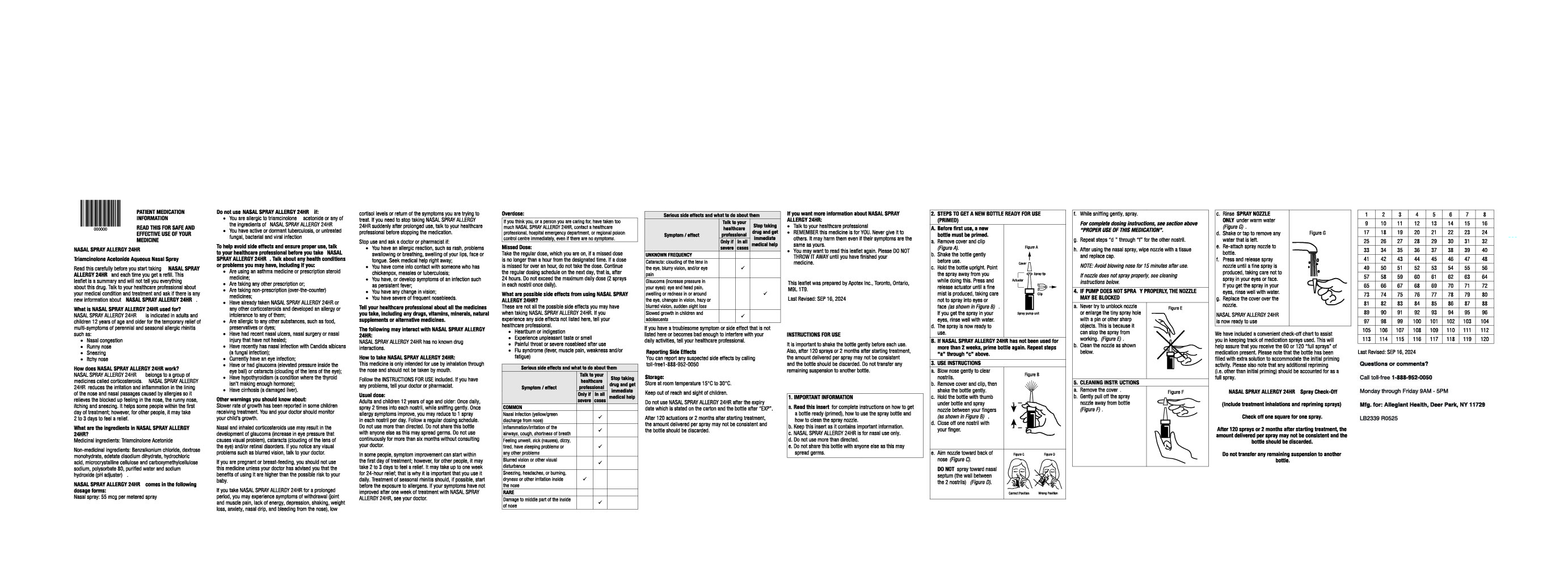 DRUG LABEL: Triamcinolone acetonide
NDC: 69168-482 | Form: SPRAY, METERED
Manufacturer: Allegiant Health
Category: otc | Type: HUMAN OTC DRUG LABEL
Date: 20250729

ACTIVE INGREDIENTS: TRIAMCINOLONE ACETONIDE 55 ug/1 1
INACTIVE INGREDIENTS: BENZALKONIUM CHLORIDE; CARBOXYMETHYLCELLULOSE SODIUM; DEXTROSE MONOHYDRATE; EDETATE DISODIUM ANHYDROUS; HYDROCHLORIC ACID; MICROCRYSTALLINE CELLULOSE; POLYSORBATE 80; WATER; SODIUM HYDROXIDE

482 - Nasal Spray Triamcinolone Acetonide

Active ingredient(s)

Triamcinolone acetonide 55 mcg (glucocorticoid)

Purpose

Allergy symptom reliever

Use(s)

temporarily relieves these symptoms due to hay fever or other upper respiratory allergies:

- nasal congestion
- runny nose
- sneezing
- itchy nose

Warnings

Do not use

- in children under 2 years of age
- if you have ever had an allergic reaction to any of the ingredients

Ask a doctor before use if you

- have had recent nose ulcers or nose surgery
- have had a nose injury that has not healed
- are using a steroid medicine for asthma, allergies or skin rash
- have an eye infection
- have or had glaucoma or cataracts

When using this product

- the growth rate of some children may be slower
- some symptoms may get better on the first day of treatment. It may take up to one week of daily use to feel the most
  symptom relief.
- do not share this bottle with anyone else as this may spread germs
- remember to tell your doctor about all the medicines you take, including this one

Stop use and ask a doctor if

- you have, or come into contact with someone who has, chickenpox, measles or tuberculosis
- you have or develop symptoms of an infection such as a persistent fever
- you have any change in vision
- you have severe or frequent nosebleeds

If pregnant or breastfeeding,

ask a health professional before use.

Keep out of reach of children

In case of overdose, get medical help or contact a Poison Control Center (1-800-222-1222) right away.

Directions

Read insert (inside package) on how to:

- get a new bottle ready (primed) before first use
- prime bottle again if not used for more than 2 weeks
- use the spray
- clean the spray nozzle

ADULTS AND CHILDREN 12 YEARS OF AGE AND OLDER
adults and children 12 years of
age and older

- once daily, spray 2 times into each nostril while sniffing gently
- once your allergy symptoms improve, reduce to 1 spray in each nostril per day

CHILDREN 2 TO UNDER 12 YEARS OF AGE

- the growth rate of some children may be slower while using this product. Talk to your child’s
  doctor if your child needs to use the spray for longer than two months a year.

Children 6 to under 12 years of age

- an adult should supervise use
- once daily spray 1 time into each nostril while sniffing gently
- if allergy symptoms do not improve, increase to 2 sprays in each nostril per day. Once allergy symptoms improve, reduce to 1 spray in each nostril per day.

Children 2 to under 6 years of age

- an adult should supervise use
- once daily, spray 1 time into each nostril while sniffing gently

Children under 2 years of age

- do not use
- do not use more than directed
- if you forget a dose, do not double the next dose
- do not spray into the eyes or mouth
- if allergy symptoms do not improve after one week, stop using and talk to a doctor
- do not use for the common cold
- shake well before each use

Other information

- TAMPER EVIDENT: DO NOT USE IF SEALS ON CARTON ARE BROKEN OR MISSING
- keep package and insert. They contain important information.
- store between 20°C to 25°C (68°F to 77°F)

Inactive ingredients

benzalkonium chloride solution (50% W/V), carboxymethylcellulose sodium, dextrose monohydrate,
edetate disodium dihydrate, hydrochloric acid, microcrystalline cellulose, polysorbate 80, purified
water & sodium hydroxide

Questions/Comments

Call 1-888-952-0050

(Monday-Friday 9 AM – 5 PM EST)

Principal Display Panel

Triamcinolone acetonide Carton
Triamcinolone acetonide Insert